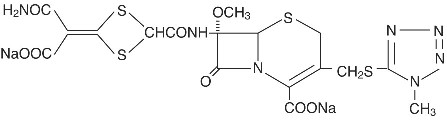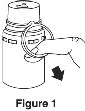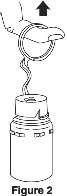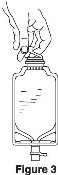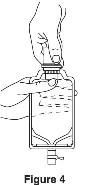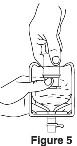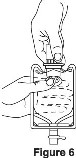 DRUG LABEL: Unknown
Manufacturer: AstraZeneca Pharmaceuticals, LP
Category: prescription | Type: Human Prescription Drug Label
Date: 20060919

CEFOTAN®
cefotetan disodium for injection
FOR INTRAVENOUS OR INTRAMUSCULAR USE
CEFOTAN®
cefotetan injection
FOR INTRAVENOUS USE ONLY

In GALAXY® Plastic Container (PL 2040)

To reduce the development of drug-resistant bacteria and maintain the effectiveness of CEFOTAN and other antibacterial drugs, CEFOTAN should be used only to treat or prevent infections that are proven or strongly suspected to be caused by bacteria.

DESCRIPTION

CEFOTAN (cefotetan disodium for injection) and CEFOTAN (cefotetan injection) in Galaxy® * plastic container (PL 2040) as cefotetan disodium are sterile, semisynthetic, broad-spectrum, beta-lactamase resistant, cephalosporin (cephamycin) antibiotics for parenteral administration. It is the disodium salt of [6R-(6α,7α)]-7-[[[4-(2-amino-1-carboxy-2-oxoethylidene)-1,3-dithietan-2-yl]carbonyl]amino]-7-methoxy-3-[[(1-methyl-1H-tetrazol-5-yl)thio]methyl]-8-oxo-5-thia-1-azabicyclo[4.2.0]oct-2-ene-2-carboxylic acid. Its molecular formula is

C17H15N7Na2O8S4 with a molecular weight of 619.57.

Structural Formula

CEFOTAN (cefotetan disodium for injection) is supplied in vials containing 80 mg (3.5 mEq) of sodium per gram of cefotetan activity. It is a white to pale yellow powder which is very soluble in water. Reconstituted solutions of CEFOTAN (cefotetan disodium for injection) are intended for intravenous and intramuscular administration. The solution varies from colorless to yellow depending on the concentration. The pH of freshly reconstituted solutions is usually between 4.5 to 6.5.

CEFOTAN in the ADD-Vantage Vial† is intended for intravenous use only after dilution with the appropriate volume of ADD-Vantage diluent solution.

CEFOTAN is available in two vial strengths. Each CEFOTAN 1 g vial contains cefotetan disodium equivalent to 1 g cefotetan activity. Each CEFOTAN 2 g vial contains cefotetan disodium equivalent to 2 g cefotetan activity.

CEFOTAN (cefotetan injection) in the Galaxy® plastic container (PL 2040) is a frozen, iso-osmotic, sterile, nonpyrogenic premixed 50 mL solution containing 1 g or 2 g cefotetan as sterile cefotetan disodium. Dextrose, USP has been added to adjust the osmolality to 300 mOsmol/kg (approximately 1.9 g and 1.1 g to the 1 g and 2 g dosages, respectively); sodium bicarbonate has been added to convert cefotetan free acid to the sodium salt. The pH has been adjusted between 4 and 6.5 with sodium bicarbonate and may have been adjusted with hydrochloric acid. CEFOTAN (cefotetan injection) in the Galaxy® plastic container (PL 2040) contains 80 mg (3.5 mEq) of sodium per gram of cefotetan activity. After thawing to room temperature, the solution is intended for intravenous use only.

This Galaxy® container is fabricated from a specially designed multilayer plastic (PL 2040). Solutions are in contact with the polyethylene layer of this container and can leach out certain chemical components of the plastic in very small amounts within the expiration dating period. The suitability of the plastic has been confirmed in tests in animals according to the USP biological tests for plastic containers as well as by tissue culture toxicity.

CLINICAL PHARMACOLOGY

High plasma levels of cefotetan are attained after intravenous and intramuscular administration of single doses to normal volunteers.

PLASMA CONCENTRATIONS AFTER 1 GRAM IV [30-minute infusion] OR IM DOSE
Mean Plasma Concentration (μg/mL)
Time After Injection
Route | 15 min | 30 min | 1h | 2h | 4h | 8h | 12h
IV | 92 | 158 | 103 | 72 | 42 | 18 | 9
IM | 34 | 56 | 71 | 68 | 47 | 20 | 9

PLASMA CONCENTRATIONS AFTER 2 GRAM IV [Injected over 3 minutes] OR IM DOSE
Mean Plasma Concentration (μg/mL)
Time After Injection
Route | 5 min | 10 min | 1h | 3h | 5h | 9h | 12h
IV | 237 | 223 | 135 | 74 | 48 | 22 | 12 [Concentrations estimated from regression line]
IM | -- | 20 | 75 | 91 | 69 | 33 | 19

The plasma elimination half-life of cefotetan is 3 to 4.6 hours after either intravenous or intramuscular administration.

Repeated administration of CEFOTAN does not result in

accumulation of the drug in normal subjects.

Cefotetan is 88% plasma protein bound.

No active metabolites of cefotetan have been detected; however, small amounts (less than 7%) of cefotetan in plasma and urine may be converted to its tautomer, which has antimicrobial activity similar to the parent drug.

In normal patients, from 51% to 81% of an administered dose of CEFOTAN is excreted unchanged by the kidneys over a 24 hour period, which results in high and prolonged urinary concentrations. Following intravenous doses of 1 gram and 2 grams, urinary concentrations are highest during the first hour and reach concentrations of approximately 1700 and 3500 µg/mL respectively.

In volunteers with reduced renal function, the plasma half-life of cefotetan is prolonged. The mean terminal half-life increases with declining renal function, from approximately 4 hours in volunteers with normal renal function to about 10 hours in those with moderate renal impairment. There is a linear correlation between the systemic clearance of cefotetan and creatinine clearance. When renal function is impaired, a reduced dosing schedule based on creatinine clearance must be used. (see DOSAGE AND ADMINISTRATION).

In pharmacokinetics studies of eight elderly patients (greater than 65 years) with normal renal function and six healthy volunteers (aged 25 to 28 years), mean (± 1sd) Total Body Clearance (1.8(0.1) L/h vs. 1.8 (0.3) L/h) and mean Volume of Distribution (10.4(1.2) L vs. 10.3 (1.6)L) were similar following administration of a one gram intravenous bolus dose.

Therapeutic levels of cefotetan are achieved in many body tissues and fluids including:

skin | ureter
muscle | bladder
fat | maxillary sinus mucosa
myometrium | tonsil
endometrium | bile
cervix | peritoneal fluid
ovary | umbilical cord serum
kidney | amniotic fluid

Microbiology

The bactericidal action of cefotetan results from inhibition of cell wall synthesis. Cefotetan has in vitro activity against a wide range of aerobic and anaerobic gram-positive and gram-negative organisms. The methoxy group in the 7-alpha position provides cefotetan with a high degree of stability in the presence of beta-lactamases including both penicillinases and cephalosporinases of gram-negative bacteria.

Cefotetan has been shown to be active against most strains of the following organisms both in vitro and in clinical infections (see INDICATIONS AND USAGE).

Gram-Negative Aerobes

Escherichia coli

Haemophilus influenzae (including ampicillin-resistant strains)

Klebsiella species (including K. pneumoniae)

Morganella morganii

Neisseria gonorrhoeae (nonpenicillinase-producing strains)

Proteus mirabilis

Proteus vulgaris

Providencia rettgeri

Serratia marcescens

NOTE: Approximately one-half of the usually clinically significant strains of Enterobacter species (eg, E. aerogenes and E. cloacae) are resistant to cefotetan. Most strains of Pseudomonas aeruginosa and Acinetobacter species are resistant to cefotetan.

Gram-Positive Aerobes

Staphylococcus aureus (including penicillinase- and

nonpenicillinase-producing strains)

Staphylococcus epidermidis

Streptococcus agalactiae (group B beta-hemolytic streptococcus)

Streptococcus pneumoniae

Streptococcus pyogenes

NOTE: Methicillin-resistant staphylococci are resistant to cephalosporins. Some strains of Staphylococcus epidermidis and most strains of enterococci, eg, Enterococcus faecalis (formerly Streptococcus faecalis) are resistant to cefotetan

Anaerobes

Prevotella bivia (formerly Bacteroides bivius)

Prevotella disiens (formerly Bacteroides disiens)

Bacteroides fragilis

Prevotella melaninogenica (formerly Bacteroides

melaninogenicus)

Bacteroides vulgatus

Fusobacterium species

Gram-positive bacilli (including Clostridium species; seeWARNINGS)

NOTE: Most strains of C. difficile are resistant (see WARNINGS).

Peptococcus niger

Peptostreptococcus species

NOTE: Many strains of B. distasonis, B. ovatus and B. thetaiotaomicron are resistant to cefotetan in vitro. However, the therapeutic utility of cefotetan against these organisms cannot be accurately predicted on the basis of in vitro susceptibility tests alone.

The following in vitro data are available but their clinical significance is unknown. Cefotetan has been shown to be active in vitro against most strains of the following organisms:

Gram-Negative Aerobes

Citrobacter species (including C. diversus and C. freundii)

Klebsiella oxytoca

Moraxella (Branhamella) catarrhalis

Neisseria gonorrhoeae (penicillinase-producing strains)

Salmonella species

Serratia species

Shigella species

Yersinia enterocolitica

Anaerobes

Porphyromonas asaccharolytica (formerly Bacteroides

asaccharolyticus)

Prevotella oralis (formerly Bacteroides oralis)

Bacteroides splanchnicus

Clostridium difficile (see WARNINGS)

Propionibacterium species

Veillonella species

Susceptibility Tests

Dilution Techniques: Quantitative methods are used to determine antimicrobial minimal inhibitory concentrations (MIC’s). These MIC’s provide estimates of the susceptibility of bacteria to antimicrobial compounds. The MICs should be determined using a standardized procedure. Standardized procedures are based on a dilution method^1 (broth or agar) or equivalent with standardized inoculum concentrations and standardized concentrations or cefotetan powder. The MIC values should be interpreted according to the following criteria:

MIC (μg/mL) | Interpretation
≤ 16 | Susceptible (S)
32 | Intermediate (I)
≥ 64 | Resistant (R)

A report of ‘Susceptible’ indicates that the pathogen is likely to be inhibited if the antimicrobial compound in the blood reaches the concentrations usually achievable. A report of ‘Intermediate’ indicates that the result should be considered equivocal, and if the microorganism is not fully susceptible to alternative, clinically feasible drugs, the test should be repeated. This category implies possible clinical applicability in body sites where the drug is physiologically concentrated or in situations where high dosage of drug can be used. This category also provides a buffer zone which prevents small uncontrolled technical factors from causing major discrepancies in interpretation. A report of ‘Resistant’ indicates that the pathogen is not likely to be inhibited if the antimicrobial compound in the blood reaches the concentrations usually achievable; other therapy should be selected.

Standardized susceptibility test procedures require the use of laboratory control microorganisms to control the technical aspects of the laboratory procedures. Standard cefotetan powder should provide the following MIC values:

Microorganism | MIC (μg/mL)
E. coli ATCC 25922 | 0.06-0.25
S. aureus ATCC 29213 | 4-16

Diffusion Techniques: Quantitative methods that require measurement of zone diameters also provide reproducible estimates of the susceptibility of bacteria to antimicrobial compounds. One such standardized procedure^2 requires the use of the standardized inoculum concentrations. This procedure uses paper disks impregnated with 30 μg cefotetan to test the susceptibility of microorganisms to cefotetan.

Reports from the laboratory providing results of the standard single-disk susceptibility test with a 30 µg cefotetan disk should be interpreted according to the following criteria:

Zone Diameter (mm) | Interpretation
≥ 16 | Susceptible (S)
13-15 | Intermediate (I)
≤ 12 | Resistant (R)

Interpretation should be as stated above for results using dilution techniques. Interpretation involves correlation of the diameter obtained in the disk test with the MIC for cefotetan.

As with standardized dilution techniques, diffusion methods require the use of laboratory control microorganisms that are used to control the technical aspects of the laboratory procedures. For the diffusion technique, the 30 μg cefotetan disk should provide the following zone diameters in these laboratory test quality control strains.

Microorganism | Zone Diameter (mm)
E. coli ATCC 25922 | 28-34
S. aureus ATCC 25923 | 17-23

Anaerobic Techniques: For anaerobic bacteria, the susceptibility to cefotetan as MIC’s can be determined by standardized test methods^3. The MIC values obtained should be interpreted according to the following criteria:

MIC (µg/mL) | Interpretation
≤ 16 | Susceptible (S)
32 | Intermediate (I)
≥ 64 | Resistant (R)

Interpretation is identical to that stated above for results using dilution techniques.

As with other susceptibility techniques, the use of laboratory control microorganisms is required to control the technical aspects of the laboratory standardized procedures. Standardized cefotetan powder should provide the following MIC values:

Microorganism | MIC (µg/mL)
Bacteroides fragilis ATCC 25285 | 4-16
Bacteroides thetaiotaomicron ATCC 29741 | 32-128
Eubacterium lentum ATCC 43055 | 32-128

INDICATIONS AND USAGE

To reduce the development of drug-resistant bacteria and maintain the effectiveness of CEFOTAN and other antibacterial drugs, CEFOTAN should be used only to treat or prevent infections that are proven or strongly suspected to be caused by susceptible bacteria. When culture and susceptibility information are available, they should be considered in selecting or modifying antimicrobial therapy. In the absence of such data, local epidemiology and susceptibility patterns may contribute to the empiric selection of therapy.

Treatment

CEFOTAN is indicated for the therapeutic treatment of the following infections when caused by susceptible strains of the designated organisms:

Gynecologic Infections caused by Staphylococcus aureus, (including penicillinase- and nonpenicillinase-producing strains), Staphylococcus epidermidis, Streptococcus species (excluding enterococci), Streptococcus agalactiae, E. coli, Proteus mirabilis, Neisseria gonorrhoeae, Bacteroides species (excluding B. distasonis, B. ovatus, B. thetaiotaomicron), Fusobacterium species*, and gram-positive anaerobic cocci (including Peptococcus niger and Peptostreptococcus species).

Cefotetan, like other cephalosporins, has no activity against

Chlamydia trachomatis. Therefore, when cephalosporins are used in the treatment of pelvic inflammatory disease, and C. trachomatis is one of the suspected pathogens, appropriate antichlamydial coverage should be added.

Bone and Joint Infections caused by Staphylococcus aureus.*

*Efficacy for this organism in this organ system was studied in fewer than ten infections.

Specimens for bacteriological examination should be obtained in order to isolate and identify causative organisms and to determine their susceptibilities to cefotetan. Therapy may be instituted before results of susceptibility studies are known; however, once these results become available, the antibiotic treatment should be adjusted accordingly.

In cases of confirmed or suspected gram-positive or gram-negative sepsis or in patients with other serious infections in which the causative organism has not been identified, it is possible to use CEFOTAN concomitantly with an aminoglycoside. Cefotetan combinations with aminoglycosides have been shown to be synergistic in vitro against many Enterobacteriaceae and also some other gram-negative bacteria. The dosage recommended in the labeling of both antibiotics may be given and depends on the severity of the infection and the patient's condition.

NOTE: Increases in serum creatinine have occurred when CEFOTAN was given alone. If CEFOTAN and an aminoglycoside are used concomitantly, renal function should be carefully monitored, because nephrotoxicity may be potentiated.

Prophylaxis

The preoperative administration of CEFOTAN may reduce the incidence of certain postoperative infections in patients undergoing surgical procedures that are classified as clean contaminated or potentially contaminated (eg, cesarean section, abdominal or vaginal hysterectomy, transurethral surgery, biliary tract surgery, and gastrointestinal surgery).

If there are signs and symptoms of infection, specimens for culture should be obtained for identification of the causative organism so that appropriate therapeutic measures may be initiated.

CONTRAINDICATIONS

CEFOTAN is contraindicated in patients with a known allergy to the cephalosporin group of antibiotics and in those individuals who have experienced a cephalosporin associated hemolytic anemia.

WARNINGS

BEFORE THERAPY WITH CEFOTAN IS INSTITUTED, CAREFUL INQUIRY SHOULD BE MADE TO DETERMINE WHETHER THE PATIENT HAS HAD PREVIOUS HYPERSENSITIVITY REACTIONS TO CEFOTETAN DISODIUM, CEPHALOSPORINS, PENICILLINS, OR OTHER DRUGS. IF THIS PRODUCT IS TO BE GIVEN TO PENICILLIN-SENSITIVE PATIENTS, CAUTION SHOULD BE EXERCISED BECAUSE CROSS-HYPERSENSITIVITY AMONG BETA-LACTAM ANTIBIOTICS HAS BEEN CLEARLY DOCUMENTED AND MAY OCCUR IN UP TO 10% OF PATIENTS WITH A HISTORY OF PENICILLIN ALLERGY. IF AN ALLERGIC REACTION TO CEFOTAN OCCURS, DISCONTINUE THE DRUG. SERIOUS ACUTE HYPERSENSITIVITY REACTIONS MAY REQUIRE TREATMENT WITH EPINEPHRINE AND OTHER EMERGENCY MEASURES, INCLUDING OXYGEN, INTRAVENOUS FLUIDS, INTRAVENOUS ANTIHISTAMINES, CORTICOSTEROIDS, PRESSOR AMINES, AND AIRWAY MANAGEMENT, AS CLINICALLY INDICATED.

AN IMMUNE MEDIATED HEMOLYTIC ANEMIA HAS BEEN OBSERVED IN PATIENTS RECEIVING CEPHALOSPORIN CLASS ANTIBIOTICS. SEVERE CASES OF HEMOLYTIC ANEMIA, INCLUDING FATALITIES, HAVE BEEN REPORTED IN ASSOCIATION WITH THE ADMINISTRATION OF CEFOTETAN. SUCH REPORTS ARE UNCOMMON. THERE APPEARS TO BE AN INCREASED RISK OF DEVELOPING HEMOLYTIC ANEMIA ON CEFOTETAN RELATIVE TO OTHER CEPHALOSPORINS OF AT LEAST 3 FOLD. IF A PATIENT DEVELOPS ANEMIA ANYTIME WITHIN 2-3 WEEKS SUBSEQUENT TO THE ADMINISTRATION OF CEFOTETAN, THE DIAGNOSIS OF A CEPHALOSPORIN ASSOCIATED ANEMIA SHOULD BE CONSIDERED AND THE DRUG STOPPED UNTIL THE ETIOLOGY IS DETERMINED WITH CERTAINTY. BLOOD TRANSFUSIONS MAY BE CONSIDERED AS NEEDED (See CONTRAINDICATIONS).

PATIENTS WHO RECEIVE COURSES OF CEFOTETAN FOR THE TREATMENT OR PROPHYLAXIS OF INFECTIONS SHOULD HAVE PERIODIC MONITORING FOR SIGNS AND SYMPTOMS OF HEMOLYTIC ANEMIA INCLUDING A MEASUREMENT OF HEMATOLOGICAL PARAMETERS WHERE APPROPRIATE.

Pseudomembranous colitis has been reported with nearly all antibacterial agents, including cefotetan, and may range in severity from mild to life-threatening. Therefore, it is important to consider this diagnosis in patients who present with diarrhea subsequent to the administration of antibacterial agents.

Treatment with antibacterial agents alters the normal flora of the colon and may permit overgrowth of clostridia. Studies indicate that a toxin produced by Clostridium difficile is a primary cause of “antibiotic-associated colitis”.

After the diagnosis of pseudomembranous colitis has been established, appropriate therapeutic measures should be initiated. Mild cases of pseudomembranous colitis usually respond to drug discontinuation alone. In moderate to severe cases, consideration should be given to management with fluids and electrolytes, protein supplementation, and treatment with an antibacterial drug clinically effective against Clostridium difficile colitis. (See ADVERSE REACTIONS.)

In common with many other broad-spectrum antibiotics, CEFOTAN may be associated with a fall in prothrombin activity and, possibly, subsequent bleeding. Those at increased risk include patients with renal or hepatobiliary impairment or poor nutritional state, the elderly, and patients with cancer. Prothrombin time should be monitored and exogenous vitamin K administered as indicated.

PRECAUTIONS

General:

Prescribing CEFOTANin the absence of a proven or strongly suspected bacterial infection of a prophylactic indication is unlikely to provide benefit to the patient and increases the risk of the development of drug-resistant bacteria.

As with other broad-spectrum antibiotics, prolonged use of CEFOTAN may result in overgrowth of nonsusceptible organisms. Careful observation of the patient is essential. If superinfection does occur during therapy, appropriate measures should be taken.

CEFOTAN should be used with caution in individuals with a history of gastrointestinal disease, particularly colitis.

Information for Patients:

Patients should be counseled that antibacterial drugs, including CEFOTAN, should only be used to treat bacterial infections. They do not treat viral infections (eg, the common cold). When CEFOTANis prescribed to treat a bacterial infection, patients should be told that although it is common to feel better early in the course of therapy, the medication should be taken exactly as directed. Skipping doses or not completing the full course of therapy may (1) decrease the effectiveness of the immediate treatment, and (2) increase the likelihood that bacteria will develop resistance and will not be treatable by CEFOTANor other antibacterial drugs in the future.

As with some other cephalosporins, a disulfiram-like reaction characterized by flushing, sweating, headache, and tachycardia may occur when alcohol (beer, wine, etc.) is ingested within 72 hours after CEFOTAN administration. Patients should be cautioned about the ingestion of alcoholic beverages following the administration of CEFOTAN.

Drug Interactions:

Increases in serum creatinine have occurred when CEFOTAN was given alone. If CEFOTAN and an aminoglycoside are used concomitantly, renal function should be carefully monitored, because nephrotoxicity may be potentiated.

Drug/Laboratory Test Interactions:

The administration of CEFOTAN may result in a false positive reaction for glucose in the urine using Clinitest®‡, Benedict's solution, or Fehling's solution. It is recommended that glucose tests based on enzymatic glucose oxidase be used.

As with other cephalosporins, high concentrations of cefotetan may interfere with measurement of serum and urine creatinine levels by Jaffe´ reaction and produce false increases in the levels of creatinine reported.

Carcinogenesis, Mutagenesis, Impairment of Fertility:

Although long-term studies in animals have not been performed to evaluate carcinogenic potential, no mutagenic potential of cefotetan was found in standard laboratory tests.

Cefotetan has adverse effects on the testes of prepubertal rats. Subcutaneous administration of 500 mg/kg/day (approximately 8-16 times the usual adult human dose) on days 6-35 of life (thought to be developmentally analogous to late childhood and prepuberty in humans) resulted in reduced testicular weight and seminiferous tubule degeneration in 10 of 10 animals. Affected cells included spermatogonia and spermatocytes; Sertoli and Leydig cells were unaffected. Incidence and severity of lesions were dose-dependent; at 120 mg/kg/day (approximately 2-4 times the usual human dose) only 1 of 10 treated animals was affected, and the degree of degeneration was mild.

Similar lesions have been observed in experiments of comparable design with other methylthiotetrazole-containing antibiotics and impaired fertility has been reported, particularly at high dose levels. No testicular effects were observed in 7-week-old rats treated with up to 1000 mg/kg/day SC for 5 weeks, or in infant dogs (3 weeks old) that received up to 300 mg/kg/day IV for 5 weeks. The relevance of these findings to humans is unknown.

Pregnancy:

Teratogenic Effects: Pregnancy Category B:

Reproduction studies have been performed in rats and monkeys at doses up to 20 times the human dose and have revealed no evidence of impaired fertility or harm to the fetus due to cefotetan. There are, however, no adequate and well-controlled studies in pregnant women. Because animal reproductive studies are not always predictive of human response, this drug should be used during pregnancy only if clearly needed.

Nursing Mothers:

Cefotetan is excreted in human milk in very low concentrations. Caution should be exercised when cefotetan is administered to a nursing woman.

Pediatric Use:

Safety and effectiveness in children have not been established.

Geriatric Use:

Of the 925 subjects who received cefotetan in clinical studies, 492 (53%) were 60 years and older, while 76 (8%) were 80 years and older. No overall differences in safety or effectiveness were observed between these subjects and younger subjects, and the other reported clinical experience has not identified differences in responses between elderly and younger patients, but greater sensitivity of some older individuals cannot be ruled out.

This drug is known to be substantially excreted by the kidney, and the risk of toxic reactions to this drug may be greater in patients with impaired renal function. Because elderly patients are more likely to have decreased renal function, care should be taken in dose selection, and it may be useful to monitor renal function. (See DOSAGE AND ADMINISTRATION− Impaired Renal Function).

ADVERSE REACTIONS

In clinical studies, the following adverse effects were considered related to CEFOTAN therapy. Those appearing in italics have been reported during postmarketing experience.

Gastrointestinal:

Symptoms occurred in 1.5% of patients, the most frequent were diarrhea (1 in 80) and nausea (1 in 700); pseudomembranous colitis. Onset of pseudomembranous colitis symptoms may occur during or after antibiotic treatment or surgical prophylaxis. (See WARNINGS.)

Hematologic:

Laboratory abnormalities occurred in 1.4% of patients and included eosinophilia (1 in 200), positive direct Coombs’ test (1 in 250), and thrombocytosis (1 in 300); agranulocytosis, hemolytic anemia, leukopenia, thrombocytopenia, and prolonged prothrombin time with or without bleeding.

Hepatic:

Enzyme elevations occurred in 1.2% of patients and included a rise in ALT (SGPT) (1 in 150), AST (SGOT) (1 in 300), alkaline phosphatase (1 in 700), and LDH (1 in 700).

Hypersensitivity:

Reactions were reported in 1.2% of patients and included rash (1 in 150) and itching (1 in 700); anaphylactic reactions and urticaria.

Local:

Effects were reported in less than 1% of patients and included phlebitis at the site of injection (1 in 300), and discomfort (1 in 500).

Renal:

Elevations in BUN and serum creatinine have been reported.

Urogenital:

Nephrotoxicity has rarely been reported.

Miscellaneous:

Fever

In addition to the adverse reactions listed above which have been observed in patients treated with cefotetan, the following adverse reactions and altered laboratory tests have been reported for cephalosporin-class antibiotics: pruritus, Stevens-Johnson syndrome, erythema multiforme, toxic epidermal necrolysis, vomiting, abdominal pain, colitis, superinfection, vaginitis including vaginal candidiasis, renal dysfunction, toxic nephropathy, hepatic dysfunction including cholestasis, aplastic anemia, hemorrhage, elevated bilirubin, pancytopenia, and neutropenia.

Several cephalosporins have been implicated in triggering seizures, particularly in patients with renal impairment, when the dosage was not reduced. (See DOSAGE AND ADMINISTRATIONand OVERDOSAGE.) If seizures associated with drug therapy occur, the drug should be discontinued. Anticonvulsant therapy can be given if clinically indicated.

OVERDOSAGE

Information on overdosage with CEFOTAN in humans is not available. If overdosage should occur, it should be treated symptomatically and hemodialysis considered, particularly if renal function is compromised.

DOSAGE AND ADMINISTRATION

Cefotetan injection in Galaxy® plastic container should not be used for intramuscular administration.

CEFOTAN in the ADD-Vantage Vial is intended for intravenous infusion only, after dilution with the appropriate volume of ADD-Vantage diluent solution.

The usual adult dosage is 1 or 2 grams of CEFOTAN (cefotetan disodium for injection) administered intravenously or intramuscularly or CEFOTAN (cefotetan injection) in the Galaxy® plastic container (PL 2040) administered intravenously every 12 hours for 5 to 10 days. Proper dosage and route of administration should be determined by the condition of the patient, severity of the infection, and susceptibility of the causative organism.

General Guidelines for Dosage of CEFOTAN
Type of Infection | Daily Dose | Frequency and Route
Urinary Tract | 1-4 grams | 500 mg every 12 hours IV or IM; 1 or 2 g every 24 hours IV or IM; 1 or 2 g every 12 hours IV or IM
Skin & Skin Structure; Mild - Moderate [Klebsiella pneumoniae skin and skin structure infections should be treated with 1 or 2 grams every 12 hours IV or IM.] | 2 grams | 2 g every 24 hours IV; 1 g every 12 hours IV or IM
Severe | 4 grams | 2 g every 12 hours IV
Other Sites | 2 - 4 grams | 1 or 2 g every 12 hours IV or IM
Severe | 4 grams | 2 g every 12 hours IV
Life-Threatening | 6 grams [Maximum daily dosage should not exceed 6 grams.] | 3 g every 12 hours IV

If Chlamydia trachomatis is a suspected pathogen in gynecologic infections, appropriate antichlamydial coverage should be added, since cefotetan has no activity against this organism.

Prophylaxis:

To prevent postoperative infection in clean contaminated or potentially contaminated surgery in adults, the recommended dosage is 1 or 2 g of CEFOTAN administered once, intravenously, 30 to 60 minutes prior to surgery. In patients undergoing cesarean section, the dose should be administered as soon as the umbilical cord is clamped.

Impaired Renal Function

When renal function is impaired, a reduced dosage schedule must be employed. The following dosage guidelines may be used.

DOSAGE GUIDELINES FOR PATIENTS WITH IMPAIRED RENAL FUNCTION
Creatinine; Clearance; mL/min | Dose | Frequency
>30 | Usual Recommended Dosage [Dose determined by the type and severity of infection, and susceptibility of the causative organism] | Every 12 hours
10 - 30 | Usual Recommended Dosage | Every 24 hours
<10 | Usual Recommended Dosage | Every 48 hours

Alternatively, the dosing interval may remain constant at 12 hour intervals, but the dose reduced to one-half the usual recommended dose for patients with a creatinine clearance of 10-30 mL/min, and one-quarter the usual recommended dose for patients with a creatinine clearance of less than 10 mL/min.

When only serum creatinine levels are available, creatinine clearance may be calculated from the following formula. The serum creatinine level should represent a steady state of renal function.

Males:Weight (kg) x (140 - age)

72 x serum creatinine (mg/100 mL)

Females:0.9 x value for males

Cefotetan is dialyzable and it is recommended that for patients undergoing intermittent hemodialysis, one-quarter of the usual recommended dose be given every 24 hours on days between dialysis and one-half the usual recommended dose on the day of dialysis.

CEFOTETAN DISODIUM FOR INJECTION

For Intravenous Use:

Reconstitute with Sterile Water for Injection. Shake to dissolve and let stand until clear.

Vial Size | Amount of; Diluent; Added; (mL) | Approximate; Withdrawable; Vol (mL) | Approximate; Average; Concentration; (mg/mL)
1 gram | 10 | 10.5 | 95
2 grams | 10-20 | 11-21 | 182-95

Infusion bottles (100 mL) may be reconstituted with 50 to 100 mL of Dextrose Injection 5% or Sodium Chloride Injection 0.9%.

NOTE: ADD-VANTAGE VIALS ARE NOT TO BE USED IN THIS MANNER

For ADD-Vantage Vials: ADD-Vantage Vials of CEFOTAN are to be reconstituted only with Sodium Chloride Injection 0.9% or Dextrose Injection 5% in the 50 mL, 100 mL or 250 mL Flexible Diluent Containers. CEFOTAN supplied in single-use ADD-Vantage Vials should be prepared as directed.

Directions for Use of CEFOTAN (cefotetan disodium for injection) in ADD-Vantage Vials:

To Open Diluent Container: Peel overwrap from the corner and remove container. Some opacity of the plastic due to moisture absorption during the sterilization process may be observed. This is normal and does not affect the solution quality or safety. The opacity will diminish gradually.

To Assemble ADD-Vantage Vial and Flexible Diluent Container: (Use Aseptic Technique)

1.Remove the protective covers from the top of the vial and the vial port on the diluent container as follows:

To remove the breakaway vial cap, swing the pull ring over the top of the vial and pull down far enough to start the opening (See Figure 1), then pull straight up to remove the cap. (See Figure 2.)

NOTE: Once the breakaway cap has been removed, do not access vial with syringe.

b.To remove the vial port cover, grasp the tab on the pull ring, pull up to break the three tie strings, then pull back to remove the cover. (See Figure 3.)

2.Screw the vial into the vial port until it will go no further. THE VIAL MUST BE SCREWED IN TIGHTLY TO ASSURE A SEAL. This occurs approximately 1/2 turn (180°) after the first audible click. (See Figure 4.) The clicking sound does not assure a seal; the vial must be turned as far as it will go. NOTE: ONCE VIAL IS SEATED, DO NOT ATTEMPT TO REMOVE. (See Figure 4.).

3.Recheck the vial to assure that it is tight by trying to turn it further in the direction of assembly.

4.Label appropriately.

To Prepare Admixture:

1.Squeeze the bottom of the diluent container gently to inflate the portion of the container surrounding the end of the drug vial.

2.With the other hand, push the drug vial down into the container telescoping the walls of the container. Grasp the inner cap of the vial through the walls of the container. (See Figure 5.)

3.Pull the inner cap from the drug vial. (See Figure 6.) Verify that the rubber stopper has been pulled out and invert the system several times, allowing the drug and diluent to mix.

4.Mix contents thoroughly and use within the specified time.

Technique)

1.Confirm the activation and admixture of vial contents.

2.Check for leaks by squeezing container firmly. If leaks are found, discard unit as sterility may be impaired.

3.Close flow control clamp of administration set.

4.Remove cover from outlet port at bottom of container.

5.Insert piercing pin of administration set into port with a twisting motion until the pin is firmly seated.

NOTE: See full directions on administration set carton.

6.Lift the free end of the hanger loop on the bottom of the vial, breaking the two tie strings. Bend the loop outward to lock it in the upright position, then suspend container from hanger.

7.Squeeze and release drip chamber to establish proper fluid level in chamber.

8.Open flow control clamp and clear air from set. Close clamp.

9.Attach set to venipuncture device. If device is not indwelling, prime and make venipuncture.

10.Regulate rate of administration with flow control clamp.

WARNING:Do not use flexible container in series connections.

For Intramuscular Use:

Reconstitute with Sterile Water for Injection; Bacteriostatic Water for Injection; Sodium Chloride Injection 0.9%, USP; 0.5% Lidocaine HCl; or 1% Lidocaine HCl. Shake to dissolve and let stand until clear.

Vial; Size | Amount of; Diluent; Added; (mL) | Approximate; Withdrawable; Vol (mL) | Approximate; Average Concentration; (mg/mL)
1 gram | 2 | 2.5 | 400
2 grams | 3 | 4 | 500

Intravenous Administration

The intravenous route is preferable for patients with bacteremia, bacterial septicemia, or other severe or life-threatening infections, or for patients who may be poor risks because of lowered resistance resulting from such debilitating conditions as malnutrition, trauma, surgery, diabetes, heart failure, or malignancy, particularly if shock is present or impending.

For intermittent intravenous administration, a solution containing 1 gram or 2 grams of CEFOTAN (cefotetan disodium for injection) in Sterile Water for Injection can be injected over a period of three to five minutes. Using an infusion system, the solution may also be given over a longer period of time through the tubing system by which the patient may be receiving other intravenous solutions. Butterfly® or scalp vein-type needles are preferred for this type of infusion. However, during infusion of the solution containing CEFOTAN (cefotetan disodium for injection), it is advisable to discontinue temporarily the administration of other solutions at the same site.

NOTE: Solutions of CEFOTAN must not be admixed with solutions containing aminoglycosides. If CEFOTAN and aminoglycosides are to be administered to the same patient, they must be administered separately and not as a mixed injection.

Intramuscular Administration

As with all intramuscular preparations, CEFOTAN (cefotetan disodium for injection) should be injected well within the body of a relatively large muscle such as the upper outer quadrant of the buttock (ie, gluteus maximus); aspiration is necessary to avoid inadvertent injection into a blood vessel.

CEFOTETAN INJECTION

Directions for Use of CEFOTAN (cefotetan injection) in Galaxy® Plastic Container (PL 2040)

CEFOTAN (cefotetan injection) in Galaxy® plastic container (PL 2040) is for intravenous administration only.

Storage:

Store in a freezer capable of maintaining a temperature of -20°C/-4°F.

Thawing of Plastic Container:

Thaw frozen container at room temperature (25°C/77°F) or in a refrigerator (5°C/41°F). [DO NOT FORCE THAW BY IMMERSION IN WATER BATHS OR BY MICROWAVE IRRADIATION.]

Check for minute leaks by squeezing container firmly. If leaks are detected, discard solution as sterility may be impaired.

The container should be visually inspected. Components of the solution may precipitate in the frozen state and will dissolve upon reaching room temperature with little or no agitation. Potency is not affected. Agitate after solution has reached room temperature. If after visual inspection the solution remains cloudy or if an insoluble precipitate is noted or if any seals or outlet ports are not intact, the container should be discarded.

Preparation of Intravenous Use (Use aseptic technique):

1.Suspend container from eyelet support.

2.Remove protector from outlet port at bottom of container.

3.Attach administration set. Refer to complete directions accompanying set.

Caution: Do not use plastic containers in series connections. Such use could result in air embolism due to residual air being drawn from the primary container before administration of the fluid from the secondary container is complete.

Intravenous Administration

The intravenous route is preferable for patients with bacteremia, bacterial septicemia, or other severe or life-threatening infections, or for patients who may be poor risks because of lowered resistance resulting from such debilitating conditions as malnutrition, trauma, surgery, diabetes, heart failure, or malignancy, particularly if shock is present or impending.

Using an infusion system, CEFOTAN (cefotetan injection) in Galaxy® plastic container (PL 2040) should be given over 20 to 60 minutes through the tubing system by which the patient may be receiving other intravenous solutions. Butterfly® or scalp vein-type needles are preferred for this type of infusion. However, during infusion of the solution containing CEFOTAN (cefotetan injection) in Galaxy® plastic container (PL 2040), it is advisable to discontinue temporarily the administration of other solutions at the same site.

Compatibility and Stability of CEFOTAN Products

Frozen samples should be thawed at room temperature before use. After the periods mentioned below, any unused solutions or frozen material should be discarded. DO NOT REFREEZE.

NOTE: Solutions of CEFOTAN must not be admixed-with solutions containing aminoglycosides. If CEFOTAN and aminoglycosides are to be administered to the same patient, they must be administered separately and not as a mixed injection. DO NOT ADD SUPPLEMENTARY MEDICATION.

CEFOTEAN DISODIUM FOR INJECTION

CEFOTAN (cefotetan disodium for injection) reconstituted as described above (PREPARATION OF SOLUTION) maintains satisfactory potency for 24 hours at room temperature (25°C/77°F), for 96 hours under refrigeration (5°C/41°F), and for at least 1 week in the frozen state (-20°C/-4°F). After reconstitution and subsequent storage in disposable glass or plastic syringes, CEFOTAN (cefotetan disodium for injection) is stable for 24 hours at room temperature and 96 hours under refrigeration.

ADD-Vantage Vials

Ordinarily, ADD-Vantage Vials should be reconstituted only when it is certain that the patient is ready to receive the drug. However, ADD-Vantage Vials of CEFOTAN reconstituted as described in Preparation of Solution, for ADD-Vantage Vials, maintains satisfactory potency for 24 hours at room temperature (25°C/77°F).

(DO NOT REFRIGERATE OR FREEZE CEFOTAN IN ADD-VANTAGE VIALS.)

CEFOTETAN INJECTION

The thawed solution in Galaxy® plastic container (PL 2040) remains chemically stable for 48 hours at room temperature (25°C/77°F) or for 21 days under refrigeration (5°C/41°F).

NOTE: Parenteral drug products should be inspected visually for particulate matter and discoloration prior to administration whenever solution and container permit.

HOW SUPPLIED

CEFOTAN (cefotetan disodium for injection) is a dry, white to pale yellow powder supplied in vials containing cefotetan disodium equivalent to 1 g and 2 g cefotetan activity for intravenous and intramuscular administration. The vials should not be stored at temperatures above 22°C (72°F) and should be protected from light.

1 g ADD-Vantage Vial (NDC 0310-0376-31)

2 g ADD-Vantage Vial (NDC 0310-0377-32)

1 g Vial (NDC 0310-0376-10)

2 g Vial (NDC 0310-0377-20)

1 g Piggyback Vial (NDC 0310-0376-11)

2 g Piggyback Vial (NDC 0310-0377-21)

CEFOTAN is also available as a 10 g pharmacy bulk package.

10 g in 100 mL Vial (NDC 0310-0375-10)

CEFOTAN (cefotetan injection) is supplied as a frozen, iso-osmotic, premixed solution in single dose Galaxy® plastic containers (PL 2040) as follows:

1 g in 50 mL plastic container (NDC 0310-0378-51)

2 g in 50 mL plastic container (NDC 0310-0379-51)

Store containers at or below -20°C/-4°F. [See DIRECTIONS FOR USE OF CEFOTAN (cefotetan injection) IN GALAXY® PLASTIC CONTAINER (PL 2040)].

REFERENCES

1.National Committee for Clinical Laboratory Standards. Methods for Dilution AntimicrobialSusceptibility Tests for Bacteria that Grow Aerobically -- Third Edition. Approved Standard NCCLS Document M7-A3, Vol. 13, No. 25, NCCLS, Villanova, PA, December, 1993.

2.National Committee for Clinical Laboratory Standards. Performance Standards for AntimicrobialDisk Susceptibility Tests -- Fifth Edition. Approved Standard NCCLS Document M2-A5, Vol. 13, No. 24, NCCLS, Villanova, PA, December 1993.

National Committee for Clinical Laboratory Standards. Methods for Antimicrobial SusceptibilityTesting of Anaerobic Bacteria - Third Edition. Approved Standard NCCLS Document M11-A3, Vol 13, No. 26, NCCLS, Villanova, PA, December 1993.

*Galaxy® is a registered trademark of Baxter Healthcare Corporation.

†ADD-Vantage is a registered trademark of Abbott Laboratories Inc.

‡Clinitest® is a registered trademark of Ames Division, Miles Laboratories, Inc.

All other trademarks are the property of the AstraZeneca group of companies.

© AstraZeneca 2002, 2004

CEFOTAN® (cefotetan injection) in Galaxy® plastic container (PL 2040) is manufactured by Baxter Healthcare Corporation, Deerfield, Illinois 60015 USA for AstraZeneca Pharmaceuticals LP.

CEFOTAN® (cefotetan disodium for injection) is manufactured by GlaxoSmithKline for:

AstraZeneca Pharmaceuticals LP, Wilmington, DE 19850

Rev 01/04 SIC 64165-03